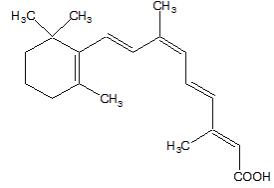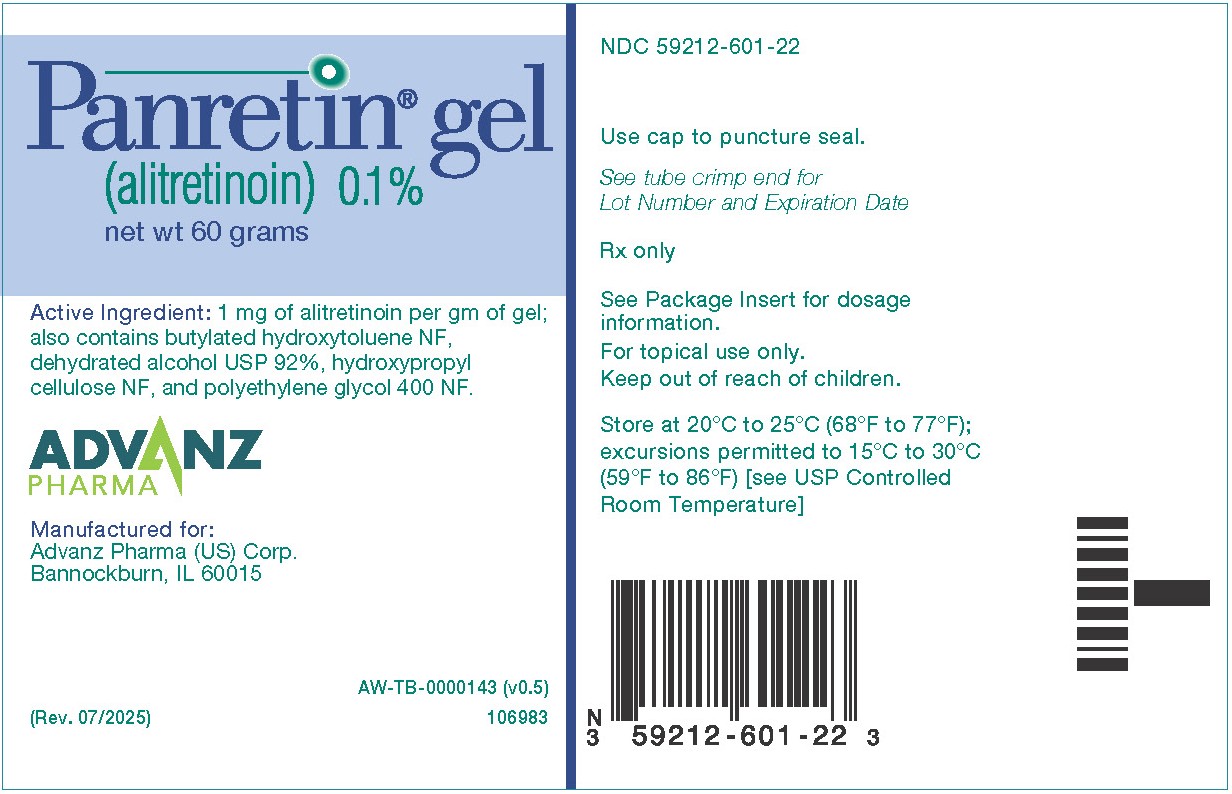 DRUG LABEL: PANRETIN
NDC: 59212-601 | Form: GEL
Manufacturer: Advanz Pharma (US) Corp.
Category: prescription | Type: Human Prescription Drug Label
Date: 20251125

ACTIVE INGREDIENTS: ALITRETINOIN 60 mg/60 g
INACTIVE INGREDIENTS: POLYETHYLENE GLYCOL 400; HYDROXYPROPYL CELLULOSE; ALCOHOL; BUTYLATED HYDROXYTOLUENE

HIGHLIGHTS OF PRESCRIBING INFORMATION

These highlights do not include all the information needed to use PANRETIN GEL safely and effectively. See full prescribing information for PANRETIN GEL.
PANRETIN GEL (alitretinoin) 0.1%, for topical use
Initial U.S. Approval: 1999

1 INDICATIONS AND USAGE

PANRETIN GEL is a retinoid indicated for the topical treatment of cutaneous lesions in adults with AIDS-related Kaposi’s sarcoma (KS).

Limitations of Use: PANRETIN GEL is not indicated when systemic anti-Kaposi’s sarcoma therapy is required.

2 DOSAGE AND ADMINISTRATION

• Apply to the affected lesions twice daily; increase to 4 times daily as tolerated. (2)
• For topical use only. (2)

3 DOSAGE FORMS AND STRENGTHS

Gel, 0.1%

4 CONTRAINDICATIONS

Hypersensitivity to retinoids or any component of PANRETIN GEL (4)

5 WARNINGS AND PRECAUTIONS

• Embryo-Fetal Toxicity: Can cause fetal harm. Advise pregnant women of the potential risk to a fetus. Advise females of reproductive potential to use an effective method of contraception. (5.1. 8.1,8.3)
• Photosensitivity: Minimize exposure to sunlight and sunlamps. (5.2)
• DEET toxicity: Do not use DEET-containing products (5.3)

6 ADVERSE REACTIONS

Most common adverse reactions (> 5%) at the application site are rash, pain, paresthesia, pruritis, exfoliative dermatitis, edema, and skin disorders. (6.1)

To report SUSPECTED ADVERSE REACTIONS, contact Advanz Pharma (US) Corp. at 1-877-370-1142 or FDA at 1-800-FDA-1088 or www.fda.gov/medwatch.

8 USE IN SPECIFIC POPULATIONS

• Pregnancy: Can cause fetal harm (8.1)
• Lactation: Advise not to breastfeed (8.2)

FULL PRESCRIBING INFORMATION

1 INDICATIONS AND USAGE

1.1 Kaposi’s Sarcoma

PANRETIN GEL is indicated for topical treatment of cutaneous lesions in adults with AIDS related Kaposi’s sarcoma (KS).

Limitations of Use: PANRETIN GEL is not indicated when systemic anti-KS therapy is required (including more than 10 new KS lesions in the prior month, symptomatic lymphedema, symptomatic pulmonary KS, or symptomatic visceral involvement) [see Clinical Studies (14.1)].

2 DOSAGE AND ADMINISTRATION

PANRETIN GEL is for topical use only.
Do not use occlusive dressings with PANRETIN GEL.

- Apply PANRETIN GEL twice daily to coat the entire cutaneous Kaposi sarcoma lesions.
- Gradually increase the application frequency up to four (4) times a day as tolerated.
- Continue PANRETIN GEL as long as patient is deriving benefit.
- Reduce application frequency for application site toxicity. Interrupt treatment for severe irritation; may resume at a reduced application frequency once symptoms improve.
- Avoid application of gel to normal skin and do not apply on or near mucosal surfaces.
- Wash hands after application unless gel is applied to Kaposi sarcoma lesions on the hands.
- Allow gel to dry for three to five minutes before covering with clothing.

3 DOSAGE FORMS AND STRENGTHS

Topical Gel: 0.1% alitretinoin (clear yellow gel) in a 60-gram tube.

4 CONTRAINDICATIONS

PANRETIN GEL is contraindicated in patients with a known hypersensitivity to retinoids or to any of the ingredients of the product.

5 WARNINGS AND PRECAUTIONS

5.1 Embryo-Fetal Toxicity

Based on data from animal studies and its mechanism of action, PANRETIN GEL can cause fetal harm when administered to a pregnant woman. Oral administration of alitretinoin to pregnant animals during the period of organogenesis was teratogenic and embryo-lethal at exposures 5 times the estimated daily human topical dose. Advise women of the potential risk to a fetus. Advise women of reproductive potential to use effective contraception during treatment with PANRETIN GEL and for 1 week after the last dose [see Use in Specific Populations (8.1, 8.3)].

5.2 Photosensitivity

Retinoids as a class have been associated with photosensitivity. Advise patients to minimize exposure of treated areas to sunlight and sunlamps during the use of PANRETIN GEL.

5.3 Toxicity with DEET-Containing Products

Animal toxicology studies showed increased DEET toxicity when DEET was included as part of the formulation. Advise patients to not use PANRETIN GEL concurrently with products that contain DEET (N,N-diethyl-m-toluamide), a common component of insect repellent products.

6 ADVERSE REACTIONS

The following clinically significant adverse reactions are described elsewhere in the labeling:
• Photosensitivity [see Warnings and Precautions (5.2)]

6.1 Clinical Trials Experience

Because clinical trials are conducted under widely varying conditions, adverse reaction rates observed in the clinical trials of a drug cannot be directly compared to rates in the clinical trials of another drug and may not reflect the rates observed in practice.

The safety of PANRETIN GEL was assessed in two multicenter, prospective, randomized, double-blind, vehicle-controlled trials (Trial 1 and Trial 2) in patients with cutaneous lesions of AIDS-related KS [see Clinical Studies (14.1)]. In a pooled analysis of both trials, the most common adverse reactions in ≥ 5% of patients were rash, pain, paresthesia, pruritis, exfoliative dermatitis, edema, and skin disorder.

In Trial 1, severe local skin adverse reactions (erythema and edema with or without vesiculation) occurred in 10% of patients during the first 12 weeks of treatment (versus 0% in the vehicle control). Adverse reactions led to withdrawal from the study in 7% of patients.

In Trial 2, severe local skin adverse reactions (erythema and edema with or without vesiculation) occurred in 6% of patients during the first 12 weeks of treatment (versus 0% in the vehicle control) and 1 patient withdrew due to severe skin irritation.

Table 1 lists the most common application site adverse reactions that occurred in a least 5% of patients during the double-blind phase who received PANRETIN GEL in either of the two controlled studies.

TABLE 1: Adverse Reactions at Application Site in Trial 1 and 2 in ≥ 5% of Patients Treated with PANRETIN GEL

Adverse Event Term | Trial 1 |  | Trial 2
 | PANRETIN GEL N=134 % | Vehicle Gel N=134 % | PANRETIN GEL N=36 % | Vehicle Gel N=46 %
Rash^1 | 77 | 11 | 25 | 4
Pain^2 | 34 | 7 | 0 | 4
Pruritus^3 | 11 | 4 | 8 | 4
Exfoliative dermatitis^4 | 9 | 2 | 3 | 0
Skin disorder^5 | 8 | 1 | 0 | 0
Edema^6 | 8 | 3 | 3 | 0
Parethesia^7 | 3 | 0 | 22 | 7
Includes Investigator terms:
^1 Erythema, scaling, irritation, redness, rash, dermatitis
^2 Burning, pain
^3 Itching, pruritus
^4 Flaking, peeling, desquamation, exfoliation
^5 Excoriation, cracking, scab, crusting, drainage, eschar, fissure or oozing
^6 Edema, swelling, inflammation
^7 Stinging, tingling

8 USE IN SPECIFIC POPULATIONS

8.1 Pregnancy

Risk Summary
Based on findings in animal studies and its mechanism of action, PANRETIN GEL can cause fetal harm when administered to a pregnant woman. Oral administration of alitretinoin to pregnant animals during the period of organogenesis was teratogenic and embryo lethal at exposures at least 5 times the estimated daily human topical dose (see Data). There are no data on the use of PANRETIN GEL in pregnant women. Advise pregnant women of the potential risk to the fetus.
In the U.S. general population, the estimated background risk of major birth defects and miscarriage in clinically recognized pregnancies is 2% to 4% and 15% to 20%, respectively.
Data
Animal Data
Oral administration of alitretinoin to pregnant rabbits during the period of organogenesis resulted in early resorptions, post-implantation loss, and fetal defects (limb, craniofacial, fused sternebrae) at doses ≥ 0.5 mg/kg/day (approximately 5 times the estimated daily human topical dose based on body surface area, assuming complete systemic absorption of alitretinoin, when PANRETIN GEL is administered as a 60 g tube over 1 month in a 60 kg human). Early resorptions and post-implantation loss also occurred in rats administered oral alitretinoin at doses ≥5 mg/kg/day (approximately 25 times the estimated daily human topical dose based on body surface area). Limb and craniofacial defects also occurred in mice administered oral alitretinoin on day 11 of gestation at single doses ≥50 mg/kg (approximately 127 times the estimated daily human topical dose based on body surface area).

8.2 Lactation

Risk Summary

It is not known whether alitretinoin or its metabolites are excreted in human milk. Because many drugs are excreted in human milk and because of the potential for adverse reactions from PANRETIN GEL in the nursing child, advise patients that breastfeeding is not recommended during treatment with PANRETIN GEL and for 1 week after the last dose.

8.3 Females and Males of Reproductive Potential

Pregnancy Testing

Verify pregnancy status of females of reproductive potential prior to initiating PANRETIN GEL.

Contraception

Females

PANRETIN GEL can cause embryo-fetal harm when administered to pregnant women [see Use in Specific Populations (8.1)]. Advise females of reproductive potential to use effective contraception during treatment with PANRETIN GEL and for 1 week after the last dose.

Males

Advise males with female partners of reproductive potential to use effective contraception during treatment with PANRETIN GEL and for 1 week after the last dose.

8.4 Pediatric Use

The safety and effectiveness of PANRETIN GEL have not been established in pediatric patients.

8.5 Geriatric Use

Clinical studies of PANRETIN GEL did not include sufficient numbers of subjects aged 65 and over to determine whether they respond differently from younger adult patients.

11 DESCRIPTION

PANRETIN GEL is a retinoid. PANRETIN GEL 0.1% contains alitretinoin and is intended for topical application only. The chemical name is (2E,4E,6Z,8E)-3,7-Dimethyl-9-(2,6,6-trimethyl-1-cyclohexen-1-yl)-2,4,6,8-nonatetraenoic acid, also known as 9-cis-retinoic acid. Chemically, alitretinoin is related to vitamin A. It is a yellow powder with a molecular weight of 300.44 and a molecular formula of C20H28O2. It is slightly soluble in ethanol (7.01 mg/g at 25℃) and insoluble in water. The structural formula of alitretinoin is as follows:

PANRETIN GEL is a clear, yellow gel containing 0.1% (w/w) alitretinoin. Each gram of PANRETIN GEL contains 1 mg alitretinoin. PANRETIN GEL contains the following inactive ingredients: butylated hydroxytoluene NF, dehydrated alcohol USP 92%, hydroxypropyl cellulose NF, and polyethylene glycol 400 NF.

12 CLINICAL PHARMACOLOGY

12.1 Mechanism of Action

Alitretinoin (9-cis-retinoic acid) is a naturally occurring endogenous retinoid that binds to and activates all known intracellular retinoid receptor subtypes (RARα, RARβ, RARγ, RXRα, RXRβ and RXRγ). Once activated these receptors function as transcription factors that regulate the expression of genes that control the process of cellular differentiation and proliferation in both normal and neoplastic cells. Alitretinoin inhibits the growth of Kaposi’s sarcoma (KS) cells in vitro.

12.2 Pharmacodynamics

Alitretinoin exposure-response relationships and the time course of pharmacodynamic response are unknown.

12.3 Pharmacokinetics

The range of 9-cis-retinoic acid plasma concentrations in patients with cutaneous lesions of AIDS-related KS after multiple daily applications of PANRETIN GEL for up to 60 weeks was similar to the range of circulating, naturally occurring 9-cis-retinoic acid plasma concentrations in untreated healthy participants.

Elimination

Metabolism

9-cis-retinoic acid is metabolized to 4-hydroxy-9-cis-retinoic acid and 4-oxo-9-cis-retinoic acid by CYP2C9, 3A4, 1A1, and 1A2. 4-oxo-9-cis-retinoic acid is the major circulating metabolite following oral administration of 9-cis-retinoic acid.

13 NONCLINICAL TOXICOLOGY

13.1 Carcinogenesis, Mutagenesis, Impairment Of Fertility

Carcinogenicity studies with alitretinoin have not been conducted. Alitretinoin was not mutagenic in vitro (bacterial assay, Chinese hamster ovary cell HGPRT mutation assay) and was not clastogenic in vitro (chromosome aberration test in human lymphocytes) or in vivo (mouse micronucleus test).

14 CLINICAL STUDIES

14.1 Kaposi’s Sarcoma

PANRETIN GEL was evaluated in two multicenter, randomized, double-blind, vehicle-controlled studies in adult patients with cutaneous lesions of AIDS-related KS. In both studies the primary efficacy objective was the patients’ cutaneous KS tumor response rate through 12 weeks of study drug treatment which was assessed by evaluating from 3 to 8 KS index lesions according to the modified AIDS Clinical Trials Group (ACTG) response criteria as applied to topical therapy (i.e., evaluation of height and area reductions of the index lesions only; progressive disease in non-index lesions and new lesions were not considered progressive disease; progressive disease was scored only in the treated index lesions). A global evaluation by physicians was also carried out. It considered all the patient’s treated lesions (index and other) compared to baseline. In this evaluation, patients with at least a 50% improvement in the KS lesions were considered responders. In addition, photographs of lesions in patients considered responders by the modified ACTG criteria were examined by the FDA for a cosmetically beneficial response, defined as at least a 50% improvement in appearance compared to baseline, considering both the KS lesions and dermal toxicity at the lesion site, in at least 50% of the index lesions and maintained for at least 3 weeks. Visceral disease was not monitored in these trials and the appearance of new KS lesions was not considered part of the response assessment.

In Trial 1, a total of 268 patients were entered from centers in the U.S. and Canada. Patients were treated topically three to four times a day with either PANRETIN GEL or a matching vehicle gel for a minimum of 12 weeks, followed by an open-label phase in patients who had not yet progressed on PANRETIN GEL. Median age of patients was 39 years, 99% were men, 75% were White, 16% Hispanic, and 7% Black. Fifty-seven percent of patients had a CD4+ lymphocyte count <200/mm3 and 36% had CD4+ lymphocyte count less than 100/mm3; 12% had visceral KS. Responses during the double-blind phase are shown in Table 2. New lesions in untreated areas were seen in about 50% of patients.

Trial 2 was an international study with a planned enrollment of 270 patients. Patients were treated topically twice a day with PANRETIN GEL or a matching vehicle for 12 weeks. The study was stopped early because of positive-interim results in the initial 82 patients. Median age of patients was 36 years for PANRETIN-GEL and 39 years for matching vehicle; all patients were men; 89% White; 5% Hispanic, and 4% Black; 67% had a CD4+ lymphocyte count ≤200/mm3 and 39% had CD4+ lymphocyte count ≤100/mm3; and 16% had visceral KS.

Results of the study are shown in Table 2. Responses to PANRETIN GEL were seen both in previously untreated patients and in patients with prior systemic and/or topical KS treatment.

Table 2: Response Rates

 | Trial 1 |  | Trial 2
 | PANRETIN GEL N=134 | Vehicle Gel N=134 | PANRETIN GEL N=36 | Vehicle Gel N=45
Modified ACTG Response | 35%* | 16% | 36% | 7%
Modified ACTG Response | P = 0.0012
Physician’s Global Subjective Assessment (all treated lesions) | 19% | 4% | 47% | 11%
Physician’s Global Subjective Assessment (all treated lesions) | P = 0.00014
Photograph Response | 15% | 4% | 19% | 2%
Photograph Response | P = 0.0026

*All responses were partial responses except 1% complete response for modified ACTG response in Trial 1.

In the clinical trials, the cumulative percentage of patients who experienced a response was less than 1% at 2 weeks, 10% at 4 weeks, and 28% at 8 weeks. Photographs of some patients revealed an erythematous and edematous response, leading to a cosmetically mixed outcome.

16 HOW SUPPLIED/STORAGE AND HANDLING

PANRETIN GEL is a clear yellow gel and is supplied in a 60-gram tubes containing 0.1% alitretinoin.
Store at 20°C to 25°C (68°F to 77°F); excursions permitted to 15°C to 30°C (59°F to 86°F) [see USP Controlled Room Temperature].
PANRETIN GEL is flammable; keep away from heat or flame.

17 PATIENT COUNSELING INFORMATION

Advise the patient to read the FDA-approved patient labeling (Patient Information).

Embryo-Fetal Toxicity

Advise females to inform their healthcare provider if they are pregnant or become pregnant. Inform females of the risk to a fetus and potential loss of pregnancy [see Warnings and Precautions (5.1) and Use in Specific Populations (8.1)].

Advise females of reproductive potential to use effective contraception during treatment and for 1 week after the last dose of PANRETIN GEL [see Warnings and Precautions (5.1) and Use in Specific Populations (8.1)].

Advise males with female partners of reproductive potential to use effective contraception during treatment and for 1 week following the last dose of PANRETIN GEL [see Warnings and Precautions (5.1) and Use in Specific Populations (8.3)].

Lactation
Advise patients not to breastfeed during treatment with PANRETIN GEL and for 1 week after the last dose of PANRETIN GEL [see Use in Specific Populations (8.2)].

Photosensitivity
Advice patients that PANRETIN GEL can cause photosensitivity and to avoid sunlight and sunlamps and use measures such as protective clothing in PANRETIN-applied areas [see Warnings and Precautions (5.2)].

Toxicity with DEET-Containing Products
Advise patients to avoid DEET-containing products such as insect repellant while using PANRETIN GEL [see Warnings and Precautions (5.3)].

Manufactured for:
Advanz Pharma (US) Corp.
Bannockburn IL, 60015
PANRETIN® is a registered trademark of Mercury Pharma Group Limited. Distributed by Advanz Pharma (US) Corp. under license

Revised: 11/2025

PATIENT INFORMATION
PANRETIN GEL (PAN-reh-tin)
(alitretinoin)

Important information: PANRETIN GEL is for use on skin (topical use) only. Do not use PANRETIN GEL in or near your eyes, inside your nose, mouth, lips, vagina, tip of the penis, rectum, or anus.

What is PANRETIN GEL?
PANRETIN GEL is a prescription medicine used to treat skin lesions in adults with AIDS-related Kaposi’s sarcoma (KS).
PANRETIN GEL is not used to treat KS when a medicine taken by mouth or injection (systemic treatment) is needed.
It is not known if PANRETIN GEL is safe and effective in children.

Do not use PANRETIN GEL if you are allergic to retinoids or any of the ingredients in PANRETIN GEL. See the end of this Patient Information leaflet for a complete list of ingredients in PANRETIN GEL.

Before using PANRETIN GEL, tell your healthcare provider about all of your medical conditions, including if you:
• are pregnant or plan to become pregnant. PANRETIN GEL can harm your unborn baby. Tell your healthcare provider right away if you become pregnant or think you may be pregnant during treatment with PANRETIN GEL.
Females who are able to become pregnant:
o Your healthcare provider should check to see if you are pregnant before you start treatment with PANRETIN GEL.
o You should use effective birth control (contraception) during treatment and for 1 week after the last dose of PANRETIN GEL.
Males with female partners who are able to become pregnant:
o You should use effective birth control (contraception) during treatment and for 1 week after the last dose of PANRETIN GEL.
• are breastfeeding or plan to breastfeed. It is not known if PANRETIN GEL passes into your breast milk. Do not breastfeed during treatment and for 1 week after your last dose of PANRETIN GEL.
Tell your healthcare provider about all the medicines you take, including prescription and over-the-counter medicines, vitamins, and herbal supplements.
Especially tell your healthcare provider about skin products that you use. You should not use products that contain DEET (N, N-diethyl-m-toluamide), during treatment with PANRETIN Gel. DEET is an ingredient commonly found in insect repellent.

How should I use PANRETIN GEL?

- Use PANRETIN GEL exactly as your healthcare provider tells you to use it.
- To open the PANRETIN GEL, remove the cap and use the point of the cap to puncture the metal safety seal.
- Apply PANRETIN GEL to affected areas 2 times a day.
- Slowly increase the number of times you apply PANRETIN GEL up to 4 times a day as tolerated.
- Cover the entire KS lesions with PANRETIN GEL.
- Avoid applying PANRETIN GEL to healthy skin around the KS lesions. Do not use PANRETIN GEL in or near the eyes, inside your nose, mouth, lips, vagina, tip of the penis, rectum or anus.
- Allow PANRETIN GEL to dry for 3 to 5 minutes before covering with clothing.
- Do not cover the treated area with bandages or dressings.
- Wash your hands with soap and water after applying PANRETIN GEL, unless PANRETIN Gel is applied to KS lesions on your hands.

What should I avoid while using PANRETIN GEL?

- Avoid sunlight and the use of sunlamps during treatment with PANRETIN GEL. PANRETIN GEL can make your skin sensitive to the sun and the light from sunlamps. Wear protective clothing that cover the treated areas if you have to be in sunlight during treatment with PANRETIN GEL.
- PANRETIN Gel is flammable. Avoid fire, flame, and smoking during and right after applying PANRETIN Gel to your skin.
- You should avoid scratching skin areas treated with PANRETIN GEL.

What are the possible side effects of PANRETIN GEL?
The most common side effects of PANRETIN GEL at the treatment site, include:

- rash
- pain
- stinging or tingling of the skin
- itching
- skin peeling or shedding
- redness or swelling
- skin cracking, scabbing, crusting, or drainage

Your healthcare provider may decrease how often you apply PANRETIN Gel or temporarily stop your treatment with PANRETIN GEL if you develop severe skin reactions.
Tell your healthcare provider about any side effect that bothers you or that does not go away.
These are not all of the possible side effects of PANRETIN GEL.
Call your doctor for medical advice about side effects. You may report side effects to FDA at 1-800-FDA-1088.

How should I store PANRETIN GEL?

- Store PANRETIN GEL at room temperature between 68°F to 77°F (20°C to 25°C).
- Keep the cap on the tube tightly closed after each use.
- Keep away from heat.

Keep PANRETIN GEL and all medicines out of the reach of children.

General information about the safe and effective use of PANRETIN GEL.
Medicines are sometimes prescribed for purposes other than those listed in a Patient Information leaflet. Do not use PANRETIN GEL for a condition for which it was not prescribed. Do not give PANRETIN GEL to other people, even if they have the same symptoms that you have. It may harm them. You can ask your pharmacist or healthcare provider for information about PANRETIN GEL that is written for health professionals.

What are the ingredients in PANRETIN GEL?
Active ingredient: alitretinoin
Inactive ingredients: butylated hydroxytoluene NF, dehydrated alcohol USP, hydroxypropyl cellulose NF, and polyethylene glycol 400 NF.
Manufactured for:
Advanz Pharma (US) Corp.
Bannockburn IL, 60015
PANRETIN® is a registered trademark of Mercury Pharma Group Limited. Distributed by Advanz Pharma (US) Corp. under license.

This patient information has been approved by the U.S. Food and Drug Administration Revise 11/2025

PACKAGE LABEL.PRINCIPAL DISPLAY PANEL

NDC 59212-601-22
Panretin® gel
(alitretinoin) 0.1%